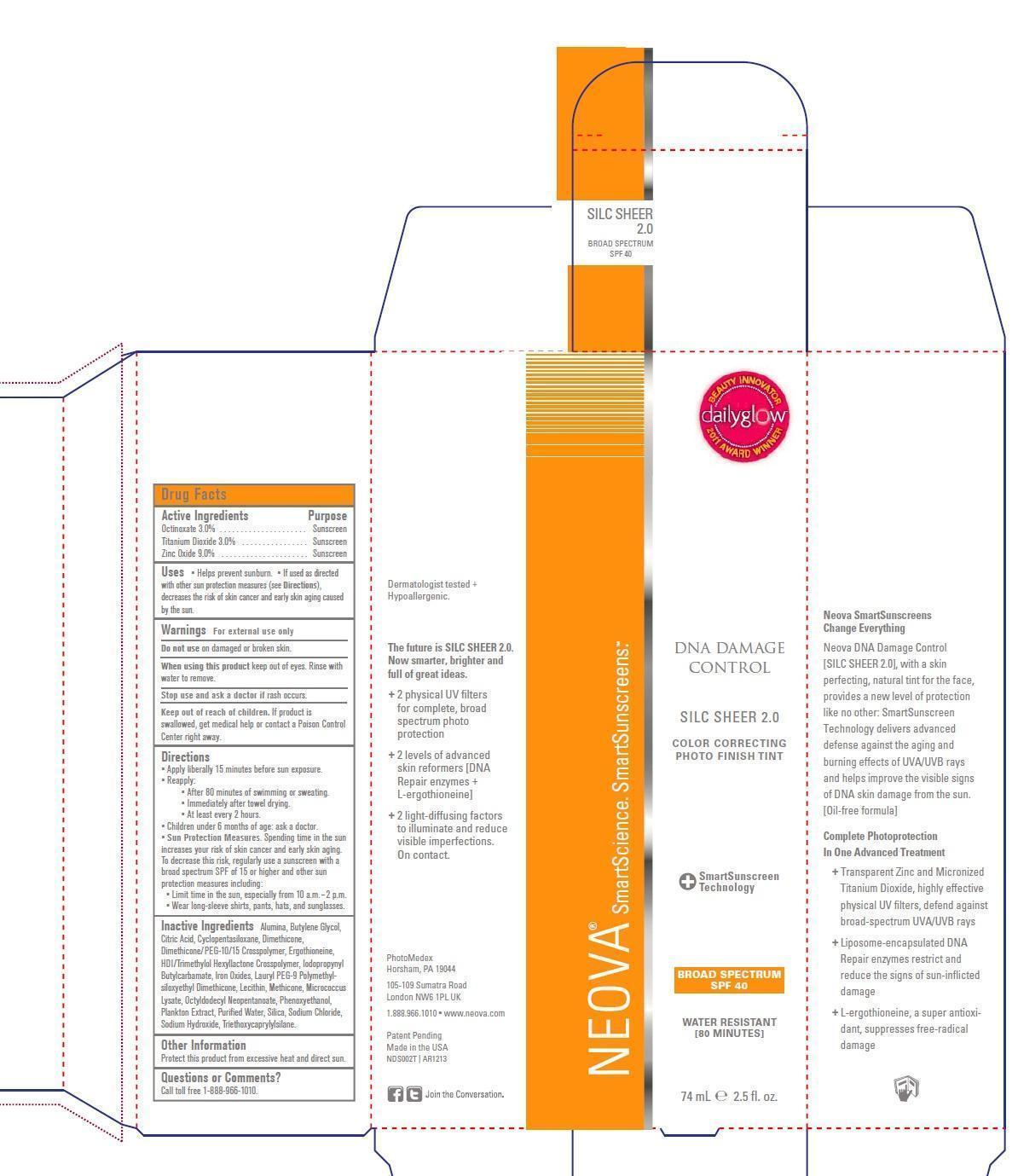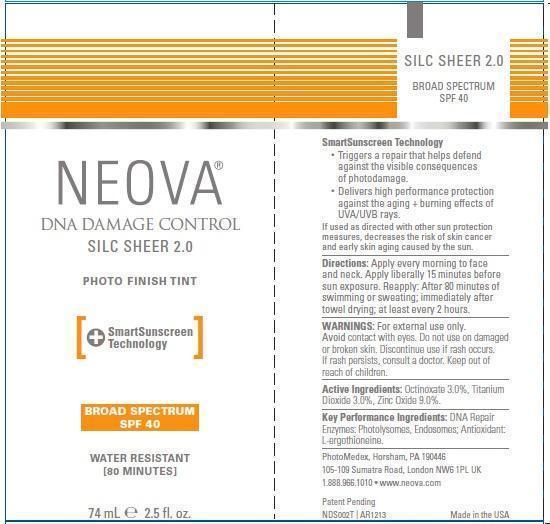 DRUG LABEL: Neova DNA Damage Control - Silc Sheer
NDC: 62362-169 | Form: EMULSION
Manufacturer: PhotoMedex, Inc.
Category: otc | Type: HUMAN OTC DRUG LABEL
Date: 20140102

ACTIVE INGREDIENTS: OCTINOXATE 3 g/100 mL; TITANIUM DIOXIDE 3 g/100 mL; ZINC OXIDE 9 g/100 mL
INACTIVE INGREDIENTS: ALUMINUM OXIDE; BUTYLENE GLYCOL; CYCLOMETHICONE 5; DIMETHICONE; ERGOTHIONEINE; IODOPROPYNYL BUTYLCARBAMATE; FERROSOFERRIC OXIDE; EGG PHOSPHOLIPIDS; OCTYLDODECANOL; PHENOXYETHANOL; WATER; SILICON DIOXIDE; SODIUM CHLORIDE; SODIUM HYDROXIDE; TRIETHOXYCAPRYLYLSILANE

Neova DNA Damage Control - Silc Sheer SPF 40 - Drug Facts

Active Ingredients

Octinoxate 3.0%, Titanium Dioxide 3.0%, Zinc Oxide 9.0%

Purpose

Sunscreen

Uses

- Helps prevent sunburn
- If used as directed and with other sun protection measures (see Directions), decreases the risk of skin cancer and early skin again caused by the sun.

Warnings

For external use only

Do not use on damaged or broken skin.

When using this product keep out of eyes. Rinse with water to remove.

Stop use and ask a doctor if rash occurs.

Keep out of reach of children. If product is swallowed, get medical help or contact a Poison Control Center right away.

Directions

- Apply liberally 15 minutes before sun exposure.
- Reapply:

°After 80 minutes of swimming or sweating.
°Immediately after towel drying.
°At least every two hours.

- Children under 6 months of age: ask a doctor.
- Sun Protection Measures. Spending time in the sun increases your risk of skin cancer and early skin aging. To decrease this risk, regularly use a sunscreen with a broad spectrum SPF of 15 or higher and other sun protection measures including:

°Limit time in the sun, especially from 10 a.m. - 2 p.m.

°Wear long-sleeve shirts, pants, hats, and sunglasses.

Inactive Ingredients

Alumina, Butylene Glycol, Citric Acid, Cyclopentasiloxane, Dimethicone, Dimethicone/PEG-10/15 Crosspolymer, Ergothioneine, HDI/Trimethylol Hexyllactone Crosspolymer, Iodopropynl Butylcarbamate, Iron Oxides, Lauryl PEG-9 Polymethylsiloxyethyl Dimethicone, Lecithin, Methicone, Micrococcus Lysate, Plankton Extract, Purified Water, Silica, Sodium Chloride, Sodium Hydroxide, Triethoxycaprylylsilane.

Other Information

Protect this product from excessive heat and direct sun.

Questions or Comments?

Call toll free 1-888-966-1010.

Neova DNA Damage Control Silc Sheer SPF 40 2.5 fl. oz. (74 mL) label and box

DNADamageControl2-5ozSilcSheerLabel.jpg DNADamageControl2-5ozSilcSheerBox.jpg